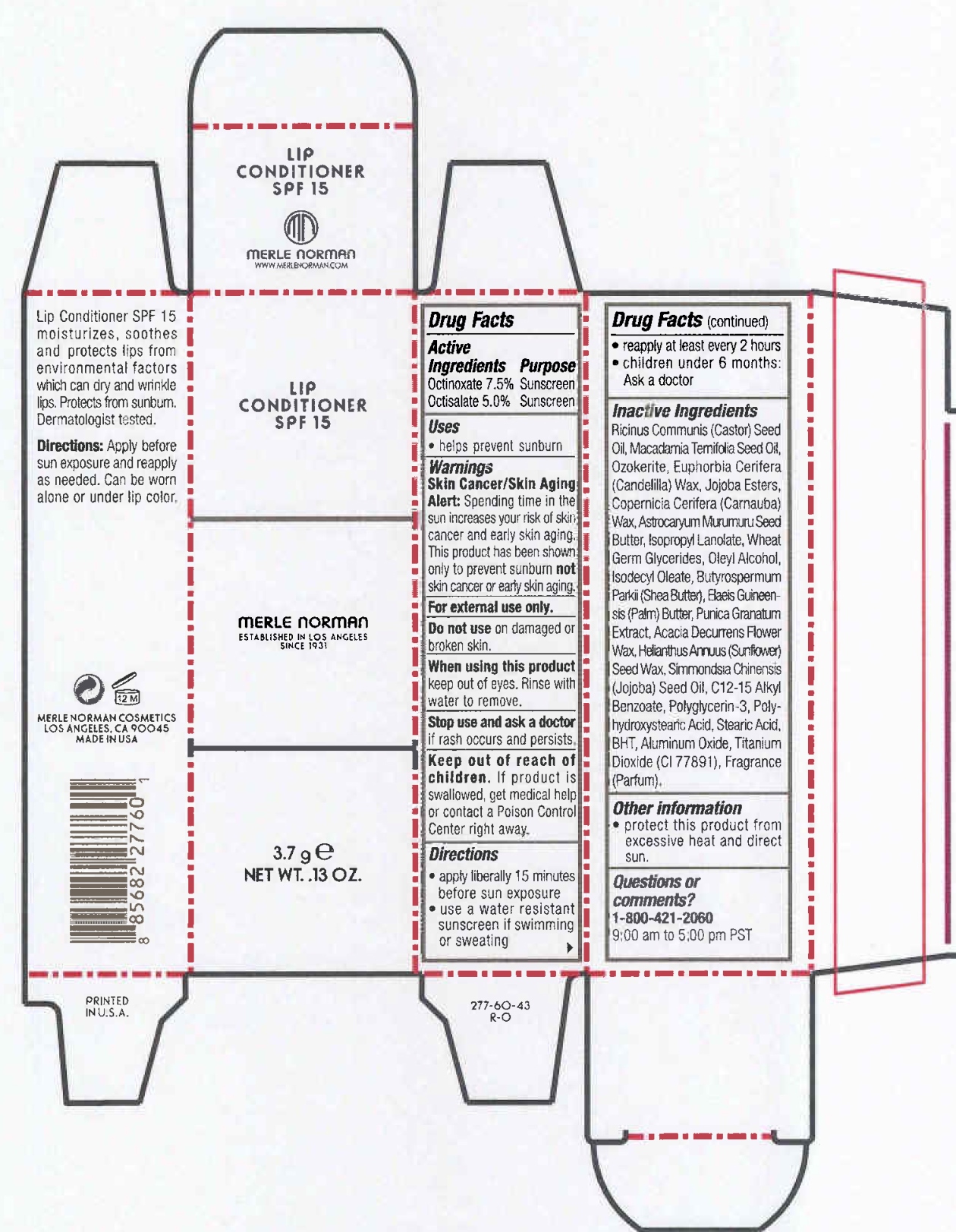 DRUG LABEL: Lip Conditioner SPF 15
NDC: 57627-107 | Form: JELLY
Manufacturer: Merle Norman Cosmetics, Inc
Category: otc | Type: HUMAN OTC DRUG LABEL
Date: 20251119

ACTIVE INGREDIENTS: OCTINOXATE 0.278 g/3.7 g; OCTISALATE 0.185 g/3.7 g
INACTIVE INGREDIENTS: CASTOR OIL; MACADAMIA OIL; CERESIN; CANDELILLA WAX; ASTROCARYUM MURUMURU SEED BUTTER; SHEA BUTTER; ELAEIS GUINEENSIS FRUIT BUTTER; HELIANTHUS ANNUUS SEED WAX; ALKYL (C12-15) BENZOATE; STEARIC ACID; BUTYLATED HYDROXYTOLUENE; ALUMINUM OXIDE; TITANIUM DIOXIDE

Merle Norman Lip Conditioner SPF 15

Active ingredients Purpose

OCTINOXATE 7.5% Sunscreen

OCTISALATE 5.0% Sunscreen

Uses
· helps prevent sunburn

· Keep out of reach of children. If product is swallowed, get medical help or
contact a Poison Control Center right away.

· Stop use and ask a doctor if rash occurs and persists

WARNINGS
Skin Cancer/Skin Aging Alert: Spending time in the sun increases your risk of skin cancer and early skin aging. This product has been shown only to help prevent sunburn, not skin cancer or early skin aging.

Warnings
· For external use only
· Do not use on damaged or broken skin
· When using this product keep out of eyes. Rinse with water to remove.

Directions
· Apply liberally 15 minutes before sun exposure
· Reapply at least every 2 hours
· Use a water resistant sunscreen if swimming or sweating
· Children under 6 months of age: Ask a doctor

Inactive

Ricinus communis (castor) seed oil, macadamia ternifolia seed oil, ozokerite, euphorbia cerifera (candelilla) wax, copernicia cerifera (carnauba) wax, astrocaryum murumuru seed butter, isopropyl lanolate, jojoba esters, wheat germ glycerides, oleyl alcohol, isodecyl oleate, butyspermum parkii (shea) butter, elaeis guineensis (palm) butter, punica granatum extract, acacia decurrens flower wax, helianthus annuus (sunflower) seed wax, simmondsia chinensis (jojoba) seed wax, jojoba oil, c12-15 alkyl benzoate, polyglyceryl-3 esters, polyhydroxystearic acid, stearic acid, BHT, aluminum oxide, titanium dioxide, Fragrance (parfum) 030411

PACKAGE LABEL

Lip Conditioner

SPF 15

Merle Norman

3.7 g net. wt. .13 oz.